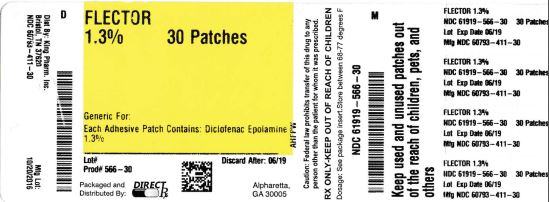 DRUG LABEL: FLECTOR
NDC: 61919-566 | Form: PATCH
Manufacturer: DIRECT RX
Category: prescription | Type: HUMAN PRESCRIPTION DRUG LABEL
Date: 20161220

ACTIVE INGREDIENTS: DICLOFENAC EPOLAMINE 180 mg/1 1
INACTIVE INGREDIENTS: METHYLPARABEN; POLYSORBATE 80; POVIDONES; WATER; PROPYLENE GLYCOL; PROPYLPARABEN; SORBITOL; BUTYLENE GLYCOL; DIHYDROXYALUMINUM AMINOACETATE; EDETATE DISODIUM; TARTARIC ACID; TITANIUM DIOXIDE; GELATIN; KAOLIN

FLECTOR

BOXED WARNING SECTION

WARNING: CARDIOVASCULAR AND GASTROINTESTINAL RISK

Cardiovascular Risk

Nonsteroidal anti-inflammatory drugs (NSAIDs) may cause an increased risk of serious cardiovascular thrombotic events, myocardial infarction, and stroke, which can be fatal. This risk may increase with duration of use. Patients with cardiovascular disease or risk factors for cardiovascular disease may be at greater risk [See Warnings and Precautions and (5.1)].

Flector Patch is contraindicated in the peri-operative setting of coronary artery bypass graft (CABG) surgery [See Contraindications (4)].

Gastrointestinal Risk

NSAIDs cause an increased risk of serious gastrointestinal adverse events including bleeding, ulceration, and perforation of the stomach or intestines, which can be fatal. These events can occur at any time during use and without warning symptoms. Elderly patients are at greater risk for serious gastrointestinal events [See Warnings and Precautions (5.2)].

INDICATIONS & USAGE SECTION

Flector® Patch is indicated for the topical treatment of acute pain due to minor strains, sprains, and contusions

DOSAGE & ADMINISTRATION SECTION

2.1 General Instructions

The recommended dose of Flector Patch is one (1) patch to the most painful area twice a day.

2.2 Special Precautions

- Patients should be informed that, if Flector Patch begins to peel-off, the edges of the patch may be taped down. If problems with adhesion persist, patients may overlay the patch with a mesh netting sleeve, where appropriate (e.g. to secure patches applied to ankles, knees, or elbows). The mesh netting sleeve (e.g. Curad® Hold Tite™, Surgilast® Tubular Elastic Dressing) must allow air to pass through and not be occlusive (non-breathable).
- Do not apply Flector Patch to non-intact or damaged skin resulting from any etiology e.g. exudative dermatitis, eczema, infected lesion, burns or wounds.
- Do not wear a Flector Patch when bathing or showering.
- Wash your hands after applying, handling or removing the patch.
- Avoid eye contact.

DOSAGE FORMS & STRENGTHS SECTION

Patch (10 × 14 cm) containing 180 mg of diclofenac epolamine, embossed with "FLECTOR PATCH <DICLOFENAC EPOLAMINE TOPICAL PATCH> 1.3%

CONTRAINDICATIONS SECTION

- Flector Patch is contraindicated in patients with a known hypersensitivity to diclofenac.
- Flector Patch is contraindicated in patients who have experienced asthma, urticaria, or allergic-type reactions after taking aspirin or other NSAIDs. Severe, rarely fatal, anaphylactic-like reactions to NSAIDs have been reported in such patients [see Warnings and Precautions (5.7, 5.13)].
- Flector Patch is contraindicated for the treatment of perioperative pain in the setting of coronary artery bypass graft (CABG) surgery [see Warnings and Precautions (5.1)].
- Flector Patch is contraindicated for use on non-intact or damaged skin resulting from any etiology, including exudative dermatitis, eczema, infection lesions, burns or wounds.

WARNINGS AND PRECAUTIONS SECTION

5.1 Cardiovascular Thrombotic Events

Clinical trials of several COX-2 selective and nonselective NSAIDs of up to three years duration have shown an increased risk of serious cardiovascular (CV) thrombotic events, myocardial infarction, and stroke, which can be fatal. All NSAIDs, both COX-2 selective and nonselective, may have a similar risk. Patients with known CV disease or risk factors for CV disease may be at greater risk. To minimize the potential risk for an adverse CV event in patients treated with an NSAID, use the lowest effective dose for the shortest duration possible. Physicians and patients should remain alert for the development of such events, even in the absence of previous CV symptoms. Inform patients about the signs and/or symptoms of serious CV events and the steps to take if they occur.

Two large, controlled, clinical trials of a COX-2 selective NSAID for the treatment of pain in the first 10-14 days following CABG surgery found an increased incidence of myocardial infarction and stroke [see Contraindications (4)].

There is no consistent evidence that concurrent use of aspirin mitigates the increased risk of serious CV thrombotic events associated with NSAID use. The concurrent use of aspirin and NSAIDs, such as diclofenac, does increase the risk of serious GI events [see Warnings and Precautions (5.2)].

5.2 Gastrointestinal Effects – Risk of GI Ulceration, Bleeding, and Perforation

NSAIDs, including diclofenac, can cause serious gastrointestinal (GI) adverse events including bleeding, ulceration, and perforation of the stomach, small intestine, or large intestine, which can be fatal. These serious adverse events can occur at any time, with or without warning symptoms, in patients treated with NSAIDs. Only one in five patients, who develop a serious upper GI adverse event on NSAID therapy, is symptomatic. Upper GI ulcers, gross bleeding, or perforation caused by NSAIDs occur in approximately 1% of patients treated for 3-6 months, and in about 2-4% of patients treated for one year. These trends continue with longer duration of use, increasing the likelihood of developing a serious GI event at some time during the course of therapy. However, even short-term therapy is not without risk.

Prescribe NSAIDs, including Flector Patch, with extreme caution in those with a prior history of ulcer disease or gastrointestinal bleeding. Patients with a prior history of peptic ulcer disease and/or gastrointestinal bleeding who use NSAIDs have a greater than 10-fold increased risk for developing a GI bleed compared to patients with neither of these risk factors. Other factors that increase the risk for GI bleeding in patients treated with NSAIDs include concomitant use of oral corticosteroids or anticoagulants, longer duration of NSAID therapy, smoking, use of alcohol, older age, and poor general health status. Most spontaneous reports of fatal GI events are in elderly or debilitated patients and therefore, special care should be taken in treating this population.

To minimize the potential risk for an adverse GI event, use the lowest effective dose for the shortest possible duration. Physicians and patients should remain alert for signs and symptoms of GI ulceration and bleeding during diclofenac therapy and promptly initiate additional evaluation and treatment if a serious GI adverse event is suspected. For high risk patients, consider alternate therapies that do not involve NSAIDs.

5.3 Hepatic Effects

Borderline elevations (less than 3 times the upper limit of the normal [ULN] range) or greater elevations of transaminases occurred in about 15% of oral diclofenac-treated patients in clinical trials of indications other than acute pain. Of the markers of hepatic function, ALT (SGPT) is recommended for the monitoring of liver injury.

In clinical trials of an oral diclofenac – misoprostol combination product, meaningful elevations (i.e., more than 3 times the ULN) of AST (SGOT) occurred in about 2% of approximately 5,700 patients at some time during diclofenac treatment (ALT was not measured in all studies).

In an open-label, controlled trial of 3,700 patients treated for 2-6 months, patients with oral diclofenac were monitored first at 8 weeks and 1,200 patients were monitored again at 24 weeks. Meaningful elevations of ALT and/or AST occurred in about 4% of the 3,700 patients and included marked elevations (>8 times the ULN) in about 1% of the 3,700 patients. In this open-label study, a higher incidence of borderline (less than 3 times the ULN), moderate (3-8 times the ULN), and marked (>8 times the ULN) elevations of ALT or AST was observed in patients receiving diclofenac when compared to other NSAIDs. Elevations in transaminases were seen more frequently in patients with osteoarthritis than in those with rheumatoid arthritis. Almost all meaningful elevations in transaminases were detected before patients became symptomatic.

Abnormal tests occurred during the first 2 months of therapy with oral diclofenac in 42 of the 51 patients in all trials who developed marked transaminase elevations. In postmarketing reports, cases of drug-induced hepatotoxicity have been reported in the first month, and in some cases, the first 2 months of therapy, but can occur at any time during treatment with diclofenac. Postmarketing surveillance has reported cases of severe hepatic reactions, including liver necrosis, jaundice, fulminant hepatitis with and without jaundice, and liver failure. Some of these reported cases resulted in fatalities or liver transplantation.

Measure transaminases (ALT and AST) periodically in patients receiving long-term therapy with diclofenac, because severe hepatotoxicity may develop without a prodrome of distinguishing symptoms. The optimum times for making the first and subsequent transaminase measurements are not known. Based on clinical trial data and postmarketing experiences, monitor transaminases within 4 to 8 weeks after initiating treatment with diclofenac. However, severe hepatic reactions can occur at any time during treatment with diclofenac.

If abnormal liver tests persist or worsen, if clinical signs and/or symptoms consistent with liver disease develop, or if systemic manifestations occur (e.g. eosinophilia, rash, abdominal pain, diarrhea, dark urine, etc.), discontinue Flector Patch immediately. To minimize the possibility that hepatic injury will become severe between transaminase measurements, inform patients of the warning signs and symptoms of hepatotoxicity (e.g., nausea, fatigue, lethargy, diarrhea, pruritus, jaundice, right upper quadrant tenderness, and "flu-like" symptoms), and the appropriate action patients should take if these signs and symptoms appear.

To minimize the potential risk for an adverse liver related event in patients treated with Flector Patch, the lowest effective dose should be used for the shortest duration possible. Exercise caution when prescribing Flector Patch with concomitant drugs that are known to be potentially hepatotoxic (e.g., acetaminophen, certain antibiotics, anti-epileptics). Caution patients to avoid taking unprescribed acetaminophen while using Flector Patch.

5.4 Hypertension

NSAIDs, including Flector Patch, can lead to new onset or worsening of pre-existing hypertension, either of which may contribute to the increased incidence of CV events. Use Flector Patch, with caution in patients with hypertension. Monitor blood pressure (BP) closely during the initiation of treatment and throughout the course of therapy.

Patients taking ACE inhibitors, thiazides or loop diuretics may have impaired response to these therapies when taking NSAIDs.

5.5 Congestive Heart Failure and Edema

Fluid retention and edema have been observed in some patients taking NSAIDs, including Flector Patch. Use Flector Patch with caution in patients with fluid retention or heart failure.

5.6 Renal Effects

Use caution when initiating treatment with Flector Patch in patients with considerable dehydration.

Long-term administration of NSAIDs has resulted in renal papillary necrosis and other renal injury. Renal toxicity has also been seen in patients in whom renal prostaglandins have a compensatory role in the maintenance of renal perfusion. In these patients, administration of an NSAID may cause a dose-dependent reduction in prostaglandin formation and, secondarily, in renal blood flow, which may precipitate overt renal decompensation. Patients at greatest risk of this reaction are those with impaired renal function, heart failure, liver dysfunction, those taking diuretics and ACE inhibitors, and the elderly. Discontinuation of NSAID therapy is usually followed by recovery to the pretreatment state.

No information is available from controlled clinical studies regarding the use of Flector Patch in patients with advanced renal disease. Therefore, treatment with Flector Patch is not recommended in these patients with advanced renal disease. If Flector Patch therapy is initiated, close monitoring of the patient's renal function is advisable.

5.7 Anaphylactic Reactions

As with other NSAIDs, anaphylactic reactions may occur both in patients with the aspirin triad and in patients without known sensitivity to NSAIDs or prior exposure to Flector Patch. Do not prescribe Flector Patch to patients with the aspirin triad. This symptom complex typically occurs in asthmatic patients who experience rhinitis with or without nasal polyps, or who exhibit severe, potentially fatal bronchospasm after taking aspirin or other NSAIDs. Anaphylaxis type reactions have been reported with NSAID products, including diclofenac products, such as Flector Patch [see Contraindications (4) and Warnings and Precautions (5.13)]. Seek emergency help in cases where an anaphylactic reaction occurs.

5.8 Skin Reactions

NSAIDs, including Flector Patch, can cause serious skin adverse events such as exfoliative dermatitis, Stevens-Johnson Syndrome (SJS), and toxic epidermal necrolysis (TEN), which can be fatal. These serious events may occur without warning. Inform patients about the signs and symptoms of serious skin manifestations, and discontinue use of the drug at the first appearance of skin rash or any other signs of hypersensitivity.

5.9 Pregnancy

Starting at 30 weeks gestation, Flector Patch, and other NSAIDs, should be avoided by pregnant women as premature closure of the ductus arteriosus in the fetus may occur [see Use in Specific Populations (8.1)].

5.10 Corticosteroid Monitoring

Flector Patch cannot be expected to substitute for corticosteroids or to treat corticosteroid insufficiency. Abrupt discontinuation of corticosteroids may lead to disease exacerbation. Slowly taper patients on prolonged corticosteroid therapy if a decision is made to discontinue corticosteroids.

5.11 Inflammation

The pharmacological activity of Flector Patch in reducing inflammation may diminish the utility of these diagnostic signs in detecting complications of presumed noninfectious, painful conditions.

5.12 Hematological Effects

Anemia is sometimes seen in patients receiving NSAIDs. This may be due to fluid retention, occult or gross GI blood loss, or an incompletely described effect upon erythropoiesis. Patients on long-term treatment with NSAIDs, including Flector Patch, should have their hemoglobin or hematocrit checked if they exhibit any signs or symptoms of anemia.

NSAIDs inhibit platelet aggregation and have been shown to prolong bleeding time in some patients. Unlike aspirin, their effect on platelet function is quantitatively less, of shorter duration, and reversible. Carefully monitor patients receiving Flector Patch who may be adversely affected by alterations in platelet function, such as those with coagulation disorders or patients receiving anticoagulants.

5.13 Preexisting Asthma

Patients with asthma may have aspirin-sensitive asthma. The use of aspirin in patients with aspirin-sensitive asthma has been associated with severe bronchospasm, which can be fatal. Since cross reactivity, including bronchospasm, between aspirin and other nonsteroidal anti-inflammatory drugs has been reported in such aspirin-sensitive patients, do not administer Flector Patch to patients with this form of aspirin sensitivity and use with caution in patients with preexisting asthma.

5.14 Accidental Exposure in Children

Even a used Flector Patch contains a large amount of diclofenac epolamine (as much as 170 mg). The potential therefore exists for a small child or pet to suffer serious adverse effects from chewing or ingesting a new or used Flector Patch. It is important for patients to store and dispose of Flector Patch out of the reach of children and pets.

5.15 Eye Exposure

Avoid contact of Flector Patch with eyes and mucosa. Advise patients that if eye contact occurs, immediately wash out the eye with water or saline and consult a physician if irritation persists for more than an hour.

5.16 Oral Nonsteroidal Anti-inflammatory Drugs

Concomitant use of oral and topical NSAIDs may result in a higher rate of hemorrhage, more frequent abnormal creatinine, urea and hemoglobin. Do not use combination therapy with Flector Patch and an oral NSAID unless the benefit outweighs the risk.

5.17 Monitoring

Because serious GI tract ulcerations and bleeding can occur without warning symptoms, monitor for signs or symptoms of GI bleeding. Check CBC and a chemistry profile periodically in patients on long-term treatment with NSAIDs. Discontinue Flector Patch if abnormal liver tests or renal tests persist or worsen.

ADVERSE REACTIONS SECTION

6.1 Clinical Studies Experience

Because clinical trials are conducted under widely varying conditions, adverse reaction rates observed in the clinical trials of a drug cannot be directly compared to rates in the clinical trials of another drug and may not reflect the rates observed in practice.

In controlled trials during the premarketing development of Flector Patch, approximately 600 patients with minor sprains, strains, and contusions have been treated with Flector Patch for up to two weeks.

Adverse Events Leading to Discontinuation of Treatment

In the controlled trials, 3% of patients in both the Flector Patch and placebo patch groups discontinued treatment due to an adverse event. The most common adverse events leading to discontinuation were application site reactions, occurring in 2% of both the Flector Patch and placebo patch groups. Application site reactions leading to dropout included pruritus, dermatitis, and burning.

Common Adverse Events

Localized Reactions

Overall, the most common adverse events associated with Flector Patch treatment were skin reactions at the site of treatment.

Table 1 lists all adverse events, regardless of causality, occurring in ≥ 1% of patients in controlled trials of Flector Patch. A majority of patients treated with Flector Patch had adverse events with a maximum intensity of "mild" or "moderate."

Table 1. Common Adverse Events (by body system and preferred term) in ≥1% of Patients treated with Flector Patch or Placebo Patch *
 | Diclofenac N=572 | Placebo N=564
N | Percent | N | Percent
Application Site Conditions | 64 | 11 | 70 | 12
Pruritus | 31 | 5 | 44 | 8
Dermatitis | 9 | 2 | 3 | <1
Burning | 2 | <1 | 8 | 1
Other † | 22 | 4 | 15 | 3
Gastrointestinal Disorders | 49 | 9 | 33 | 6
Nausea | 17 | 3 | 11 | 2
Dysgeusia | 10 | 2 | 3 | <1
Dyspepsia | 7 | 1 | 8 | 1
Other ‡ | 15 | 3 | 11 | 2
Nervous System Disorders | 13 | 2 | 18 | 3
Headache | 7 | 1 | 10 | 2
Paresthesia | 6 | 1 | 8 | 1
Somnolence | 4 | 1 | 6 | 1
Other § | 4 | 1 | 3 | <1
*The table lists adverse events occurring in placebo-treated patients because the placebo-patch was comprised of the same ingredients as Flector Patch except for diclofenac. Adverse events in the placebo group may therefore reflect effects of the non-active ingredients. †Includes: application site dryness, irritation, erythema, atrophy, discoloration, hyperhidriosis, and vesicles. ‡Includes: gastritis, vomiting, diarrhea, constipation, upper abdominal pain, and dry mouth. §Includes: hypoaesthesia, dizziness, and hyperkinesias.

Foreign labeling describes that dermal allergic reactions may occur with Flector Patch treatment. Additionally, the treated area may become irritated or develop itching, erythema, edema, vesicles, or abnormal sensation.

DRUG INTERACTIONS SECTION

7.1 Aspirin

When diclofenac is administered with aspirin, the binding of diclofenac to protein is reduced, although the clearance of free diclofenac is not altered. The clinical significance of this interaction is not known; however, as with other NSAIDs, concomitant administration of diclofenac and aspirin is not generally recommended because of the potential of increased adverse effects.

7.2 Anticoagulants

The effects of anticoagulants such as warfarin and NSAIDs on GI bleeding are synergistic, such that users of both drugs together have a risk of serious GI bleeding higher than users of either drug alone.

7.3 ACE-inhibitors

NSAIDs may diminish the antihypertensive effect of angiotensin converting enzyme (ACE) inhibitors. Consider this interaction in patients taking NSAIDs concomitantly with ACE-inhibitors.

7.4 Diuretics

Clinical studies, as well as post marketing observations, have shown that NSAIDs can reduce the natriuretic effect of furosemide and thiazides in some patients. This response has been attributed to inhibition of renal prostaglandin synthesis. During concomitant therapy with NSAIDs, observe the patient closely for signs of renal failure [see Warnings and Precautions (5.6)], as well as to assure diuretic efficacy.

7.5 Lithium

NSAIDs have produced an elevation of plasma lithium levels and a reduction in renal lithium clearance. The mean minimum lithium concentration increased 15% and the renal clearance was decreased by approximately 20%. These effects have been attributed to inhibition of renal prostaglandin synthesis by the NSAID. Thus, when NSAIDs and lithium are administered concurrently, observe patients carefully for signs of lithium toxicity.

7.6 Methotrexate

NSAIDs have been reported to competitively inhibit methotrexate accumulation in rabbit kidney slices. This may indicate that they could enhance the toxicity of methotrexate. Use caution when NSAIDs, including diclofenac, are administered concomitantly with methotrexate.

7.7 Cyclosporine

Diclofenac, like other NSAIDs, may affect renal prostaglandins and increase the toxicity of certain drugs. Therefore, concomitant therapy with diclofenac may increase cyclosporine's nephrotoxicity. Use caution when diclofenac is administered concomitantly with cyclosporine.

7.8 Oral Nonsteroidal Anti-inflammatory Drugs

Concomitant use of oral and topical NSAIDs may result in a higher rate of hemorrhage, more frequent abnormal creatinine, urea and hemoglobin. Do not use combination therapy with Flector Patch and an oral NSAID unless the benefit outweighs the risk and conduct periodic laboratory evaluations.

USE IN SPECIFIC POPULATIONS SECTION

8.1 Pregnancy

Teratogenic Effects

Pregnancy Category C prior to 30 weeks gestation; Category D starting 30 weeks gestation.

Starting at 30 weeks gestation, avoid use of Flector Patch, and other NSAIDS, in pregnant women as premature closure of the ductus arteriosus in the fetus may occur, Flector Patch can cause fetal harm when administered to a pregnant woman starting at 30 weeks gestation. If this drug is used during this time period in pregnancy, inform the patient of the potential hazard to a fetus. There are no adequate and well-controlled studies in pregnant women. Prior to 30 weeks gestation, Flector Patch should be used during pregnancy only if the potential benefit justifies the potential risk to the fetus.

Pregnant Sprague Dawley rats were administered 1, 3, or 6 mg/kg diclofenac epolamine via oral gavage daily from gestation days 6-15. Maternal toxicity, embryotoxicity, and increased incidence of skeletal anomalies were noted with 6 mg/kg/day diclofenac epolamine, which corresponds to 3-times the maximum recommended daily exposure in humans based on a body surface area comparison. Pregnant New Zealand White rabbits were administered 1, 3, or 6 mg/kg diclofenac epolamine via oral gavage daily from gestation days 6-18. No maternal toxicity was noted; however, embryotoxicity was evident at 6 mg/kg/day group which corresponds to 6.5-times the maximum recommended daily exposure in humans based on a body surface area comparison.

Nonteratogenic Effects

Male rats were orally administered diclofenac epolamine (1, 3, 6 mg/kg) for 60 days prior to mating and throughout the mating period, and females were given the same doses 14 days prior to mating and through mating, gestation, and lactation. Embryotoxicity was observed at 6 mg/kg diclofenac epolamine (3-times the maximum recommended daily exposure in humans based on a body surface area comparison), and was manifested as an increase in early resorptions, post-implantation losses, and a decrease in live fetuses. The number of live born and total born were also reduced as was F1 postnatal survival, but the physical and behavioral development of surviving F1 pups in all groups was the same as the deionized water control, nor was reproductive performance adversely affected despite a slight treatment-related reduction in body weight.

8.2 Labor and Delivery

The effects of Flector Patch on labor and delivery in pregnant women are unknown. In rat studies, maternal exposure to NSAIDs, as with other drugs known to inhibit prostaglandin synthesis, increased the incidence of dystocia, delayed parturition, and decreased pup survival.

8.3 Nursing Mothers

It is not known whether this drug is excreted in human milk. Because many drugs are excreted in human-milk and because of the potential for serious adverse reactions in nursing infants from Flector Patch, a decision should be made whether to discontinue nursing or to discontinue the drug, taking into account the importance of the drug to the mother.

8.4 Pediatric Use

Safety and effectiveness in pediatric patients have not been established.

8.5 Geriatric Use

Clinical studies of Flector Patch did not include sufficient numbers of subjects aged 65 and over to determine whether they respond differently from younger subjects. Other reported clinical experience has not identified differences in responses between the elderly and younger patients.

Diclofenac, as with any NSAID, is known to be substantially excreted by the kidney, and the risk of toxic reactions to Flector Patch may be greater in patients with impaired renal function. Because elderly patients are more likely to have decreased renal function, care should be taken when using Flector Patch in the elderly, and it may be useful to monitor renal function.

OVERDOSAGE SECTION

There is limited experience with overdose of Flector Patch. In clinical studies, the maximum single dose administered was one Flector Patch containing 180 mg of diclofenac epolamine. There were no serious adverse events.

Should systemic side effects occur due to incorrect use or accidental overdose of this product, the general measures recommended for intoxication with non-steroidal anti-inflammatory drugs should be taken.

For additional information about overdose treatment, call a poison control center (1-800-222-1222).

DESCRIPTION SECTION

FLECTOR PATCH (diclofenac epolamine patch) is a nonsteroidal anti-inflammatory drug, available for topical application. FLECTOR PATCH is a 10 cm × 14 cm patch comprised of an adhesive material containing 1.3% diclofenac epolamine which is applied to a non-woven polyester felt backing and covered with a polypropylene film release liner. The release liner is removed prior to topical application to the skin.

The chemical name of diclofenac epolamine is 2-[(2,6-dichlorophenyl) amino]benzeneacetic acid, (2-(pyrrolidin-1-yl) ethanol salt, with a molecular formula of C20H24Cl2N2O3, and molecular weight 411.3, an n-octanol/water partition coefficient of 8 at pH 8.5, and the following chemical structure:

Each adhesive patch contains 180 mg of diclofenac epolamine (13 mg per gram adhesive) in an aqueous base. It also contains the following inactive ingredients: 1,3-butylene glycol, dihydroxyaluminum aminoacetate, disodium edetate, D-sorbitol, fragrance (Dalin PH), gelatin, kaolin, methylparaben, polysorbate 80, povidone, propylene glycol, propylparaben, sodium carboxymethylcellulose, sodium polyacrylate, tartaric acid, titanium dioxide, and purified water

CLINICAL PHARMACOLOGY SECTION

12.1 Mechanism of Action

Diclofenac is a nonsteroidal anti-inflammatory drug (NSAID). In pharmacologic studies, diclofenac has shown anti-inflammatory, analgesic, and antipyretic activity. As with other NSAIDs, its mode of action is not known; its ability to inhibit prostaglandin synthesis, however, may be involved in its anti-inflammatory activity, as well as contribute to its efficacy in relieving pain associated with inflammation.

12.2 Pharmacodynamics

Flector Patch applied to intact skin provides local analgesia by releasing diclofenac epolamine from the patch into the skin.

12.3 Pharmacokinetics

Absorption

Following a single application of the Flector Patch on the upper inner arm, peak plasma concentrations of diclofenac (range 0.7 – 6 ng/mL) were noted between 10 – 20 hours of application. Plasma concentrations of diclofenac in the range of 1.3 – 8.8 ng/mL were noted after five days with twice-a-day Flector Patch application.

Systemic exposure (AUC) and maximum plasma concentrations of diclofenac, after repeated dosing for four days with Flector Patch, were lower (<1%) than after a single oral 50-mg diclofenac sodium tablet.

The pharmacokinetics of Flector Patch has been tested in healthy volunteers at rest or undergoing moderate exercise (cycling 20 min/h for 12 h at a mean HR of 100.3 bpm). No clinically relevant differences in systemic absorption were observed, with peak plasma concentrations in the range of 2.2 – 8.1 ng/mL while resting, and 2.7 – 7.2 ng/mL during exercise.

Distribution

Diclofenac has a very high affinity (>99%) for human serum albumin.

Diclofenac diffuses into and out of the synovial fluid. Diffusion into the joint occurs when plasma levels are higher than those in the synovial fluid, after which the process reverses and synovial fluid levels are higher than plasma levels. It is not known whether diffusion into the joint plays a role in the effectiveness of diclofenac.

Metabolism

Five diclofenac metabolites have been identified in human plasma and urine. The metabolites include 4'-hydroxy-, 5-hydroxy-, 3'-hydroxy-, 4',5-dihydroxy- and 3'-hydroxy-4'-methoxy diclofenac. The major diclofenac metabolite, 4'hydroxy-diclofenac, has very weak pharmacologic activity. The formation of 4'-hydroxy diclofenac is primarily mediated by CPY2C9. Both diclofenac and its oxidative metabolites undergo glucuronidation or sulfation followed by biliary excretion. Acylglucuronidation mediated by UGT2B7 and oxidation mediated by CPY2C8 may also play a role in diclofenac metabolism. CYP3A4 is responsible for the formation of minor metabolites, 5-hydroxy and 3'-hydroxy- diclofenac.

Excretion

The plasma elimination half-life of diclofenac after application of Flector Patch is approximately 12 hours. Diclofenac is eliminated through metabolism and subsequent urinary and biliary excretion of the glucuronide and the sulfate conjugates of the metabolites. Little or no free unchanged diclofenac is excreted in the urine. Approximately 65% of the dose is excreted in the urine and approximately 35% in the bile as conjugates of unchanged diclofenac plus metabolites.

NONCLINICAL TOXICOLOGY SECTION

13.1 Carcinogenesis, Mutagenesis, Impairment of Fertility

Carcinogenesis

Long-term studies in animals have not been performed to evaluate the carcinogenic potential of either diclofenac epolamine or Flector Patch.

Mutagenesis

Diclofenac epolamine is not mutagenic in Salmonella typhimurium strains, nor does it induce an increase in metabolic aberrations in cultured human lymphocytes, or the frequency of micronucleated cells in the bone marrow micronucleus test performed in rats.

Impairment of Fertility

Male and female Sprague Dawley rats were administered 1, 3, or 6 mg/kg/day diclofenac epolamine via oral gavage (males treated for 60 days prior to conception and during mating period, females treated for 14 days prior to mating through day 19 of gestation). Diclofenac epolamine treatment with 6 mg/kg/day resulted in increased early resorptions and postimplantation losses; however, no effects on the mating and fertility indices were found. The 6 mg/kg/day dose corresponds to 3-times the maximum recommended daily exposure in humans based on a body surface area comparison.

CLINICAL STUDIES SECTION

- 14.1 Ankle sprains
  Efficacy of Flector Patch was demonstrated in two of four studies of patients with minor sprains, strains, and contusions. Patients were randomly assigned to treatment with the Flector Patch, or a placebo patch identical to the Flector Patch minus the active ingredient. In the first of these two studies, patients with ankle sprains were treated once daily for a week. In the second study, patients with sprains, strains and contusions were treated twice daily for up to two weeks. Pain was assessed over the period of treatment. Patients treated with the Flector Patch experienced a greater reduction in pain as compared to patients randomized to placebo patch as evidenced by the responder curves presented below.
  Figure 1: Patients Achieving Various Levels of Pain Relief at Day 3; 14-Day Study
  Figure 2: Patients Achieving Various Levels of Pain Relief at End of Study; 14-Day Study
  Figure 3: Patients Achieving Various Levels of Pain Relief at Day 3; 7-Day Study
  Figure 4: Patients Achieving Various Levels of Pain Relief at End of Study; 7-Day Study
  Close
- 16 HOW SUPPLIED/STORAGE AND HANDLING
  The Flector Patch is supplied in resealable envelopes, each containing 5 patches (10 cm × 14 cm), with 6 envelopes per box (NDC 60793-411-30). Each individual patch is embossed with "FLECTOR PATCH <DICLOFENAC EPOLAMINE TOPICAL PATCH> 1.3%".
  - Each patch contains 180 mg of diclofenac epolamine in an aqueous base (13 mg of active per gram of adhesive or 1.3%).
  - The product is intended for topical use only.
  - Keep out of reach of children and pets.
  - ENVELOPES SHOULD BE SEALED AT ALL TIMES WHEN NOT IN USE.
  - Curad® Hold Tite™ is a trademark of Medline Industries, Inc., and Surgilast® Tubular Elastic Dressing is a trademark of Derma Sciences, Inc.
  Storage
  Store at 25ºC (77ºF); excursions permitted to 15º-30ºC (59º-86ºF) [see USP Controlled Room Temperature].
  Distributed by: King Pharmaceuticals Inc.
  501 Fifth Street
  Bristol TN 37620 USA
  Telephone: 1-888-840-8884 www.FlectorPatch.com
  Manufactured for: IBSA Institut Biochimique SA, CH-6903 Lugano, Switzerland
  Manufactured by: Teikoku Seiyaku Co., Ltd., Sanbonmatsu, Kagawa 769-2695 Japan
  FI/165 1086
  Ed. VII/08.11
  Version August, 2011

INFORMATION FOR PATIENTS SECTION

See Medication Guide

17.1 Information on Medication Guide

Inform patients of the following information before initiating therapy with an NSAID and periodically during the course of ongoing therapy. Encourage patients to read the NSAID Medication Guide that accompanies each prescription dispensed prior to using Flector Patch.

17.2 Cardiovascular Effects

Flector Patch, like other NSAIDs, may cause serious CV side effects, such as MI or stroke, which may result in hospitalization and even death. Although serious CV events can occur without warning symptoms, instruct patients to be alert for the signs and symptoms of chest pain, shortness of breath, weakness, slurring of speech, and to ask for medical advice when observing any indicative sign or symptoms. Inform patients of the importance of this follow-up [see Warnings and Precautions (5.1)].

17.3 Gastrointestinal Effects

Flector Patch, like other NSAIDs, may cause GI discomfort and, rarely, serious GI side effects, such as ulcers and bleeding, which may result in hospitalization and even death. Although serious GI tract ulcerations and bleeding can occur without warning symptoms, inform patients to be alert for the signs and symptoms of ulceration and bleeding, and to ask for medical advice when observing any indicative sign or symptoms including epigastric pain, dyspepsia, melena, and hematemesis. Instruct patients of the importance of this follow-up [see Warnings and Precautions (5.2)].

17.4 Adverse Skin Reactions

Flector Patch, like other NSAIDs, can cause serious skin side effects such as exfoliative dermatitis, SJS, and TEN, which may result in hospitalizations and even death. Although serious systemic skin reactions may occur without warning, instruct patients to be alert for the signs and symptoms of skin rash and blisters, fever, or other signs of hypersensitivity such as itching, and to ask for medical advice when observing any indicative signs or symptoms [see Warnings and Precautions (5.8)]. Advise patients to stop Flector Patch immediately if they develop any type of generalized rash and contact their physicians as soon as possible.

Flector Patch can cause a localized skin reaction at the application site. Advise patients to contact their physicians as soon as possible if they develop any type of localized application site rash.

Instruct patients not to apply Flector Patch to open skin wounds or infections.

17.5 Hepatotoxicity

Inform patients of the warning signs and symptoms of hepatotoxicity (e.g., nausea, fatigue, lethargy, pruritus, jaundice, right upper quadrant tenderness, and "flu-like" symptoms). If these occur, instruct patients to stop therapy with Flector Patch and seek immediate medical therapy [see Warnings and Precautions (5.3)].

17.6 Weight gain and edema

Patients should promptly report to their physician signs or symptoms of unexplained weight gain or edema following treatment with Flector Patch [see Warnings and Precautions (5.5)].

17.7 Anaphylactic Reactions

Inform patients of the signs of an anaphylactic reaction (e.g. difficulty breathing, swelling of the face or throat). If these occur, instruct patients to seek immediate emergency help. Anaphylaxis type reactions have been reported with diclofenac products, including Flector Patch [see Warnings and Precautions (5.7)].

17.8 Preexisting Asthma

Inform patients not to use Flector Patch if they have an aspirin-sensitive asthma. Flector Patch, like other NSAIDs, could cause severe and even fatal bronchospasm in these patients [see Warnings and Precautions (5.13)]. Instruct patients to discontinue use of Flector Patch and to immediately seek emergency help if they experience wheezing or shortness of breath.

17.9 Eye Exposure

Instruct patients to avoid contact of Flector Patch with the eyes and mucosa. Advise patients that if eye contact occurs, immediately wash out the eye with water or saline and consult a physician if irritation persists for more than an hour [see Warnings and Precautions (5.15)].

17.10 Effects during pregnancy

Starting at 30 weeks gestation, instruct patients to avoid the use of Flector Patch and other NSAIDS, as premature closure of the ductus arteriosus in the fetus may occur [see Warnings and Precautions (5.9) and Use in Specific Populations (8.1)].

17.11 General Information on Use

Instruct patients and caregivers to wash their hands after applying, handling or removing the patch.

Inform patients that, if Flector Patch begins to peel off, the edges of the patch may be taped down. If problems with adhesion persist, patients may overlay the patch with a mesh netting sleeve, where appropriate (e.g. to secure patches applied to ankles, knees, or elbows). The mesh netting sleeve (e.g. Curad® Hold Tite™, Surgilast® Tubular Elastic Dressing) must allow air to pass through and not be occlusive (non-breathable).

Instruct patients not to wear Flector Patch during bathing or showering. Bathing should take place in between scheduled patch removal and application [see Dosage and Administration (2)].

Instruct patients to store Flector Patch and to discard used patches out of the reach of children and pets. If a child or pet accidentally ingests Flector Patch, instruct patients to seek medical help immediately [see Warnings and Precautions (5.14)].

Inform patients that Flector Patch should be used only on intact skin.

Close

SPL UNCLASSIFIED SECTION

Distributed by: King Pharmaceuticals Inc

501 Fifth Street

Bristol, TN 37620 USA

Telephone: 1-888-840-8884 www.FlectorPatch.com

Manufactured for: IBSA Institut Biochimique SA, CH-6903 Lugano, Switzerland

Manufactured by: Teikoku Seiyaku Co., Ltd., Sanbonmatsu, Kagawa 769-2695 Japan

FI/165 1086

Ed. VII/08.11

Version August, 2011

SPL MEDGUIDE SECTION

Medication Guide for Non-Steroidal Anti-Inflammatory Drugs (NSAIDs)

(See the end of this Guide for a list of prescription NSAID medicines.)

What is the most important information I should know about medicines called Non-Steroidal Anti-Inflammatory Drugs (NSAIDs)?

NSAID medicines may increase the chance of a heart attack or stroke that can lead to death. This chance increases:

- with longer use of NSAID medicines
- in people who have heart disease

NSAID medicines should never be used right before or after a heart surgery called a "coronary artery bypass graft" (CABG).

NSAID medicines can cause ulcers and bleeding in the stomach and intestines at any time during treatment. Ulcers and bleeding:

- can happen without warning symptoms
- may cause death
  The chance of a person getting an ulcer or bleeding increases with:
  - taking medicines called "corticosteroids" and "anticoagulants"
  - longer use
  - smoking
  - drinking alcohol
  - older age
  - having poor health

NSAID medicines should only be used:

- exactly as prescribed
- at the lowest dose possible for your treatment
- for the shortest time needed

What are Non-Steroidal Anti-Inflammatory Drugs (NSAIDs)?

NSAID medicines are used to treat pain and redness, swelling, and heat (inflammation) from medical conditions such as:

- different types of arthritis
- menstrual cramps and other types of short-term pain

Who should not take a Non-Steroidal Anti-Inflammatory Drug (NSAID)?

Do not take an NSAID medicine:

- if you had an asthma attack, hives, or other allergic reaction with aspirin or any other NSAID medicine
- for pain right before or after heart bypass surgery

Tell your healthcare provider:

- about all of your medical conditions.
- about all of the medicines you take. NSAIDs and some other medicines can interact with each other and cause serious side effects. Keep a list of your medicines to show to your healthcare provider and pharmacist.
- if you are pregnant, NSAID medicines should not be used past 30 weeks of pregnancy..
- if you are breastfeeding, talk to your doctor.

What are the possible side effects of Non-Steroidal Anti-Inflammatory Drugs (NSAIDs)?

Serious side effects include: | Other side effects include:
- heart attack - stroke - high blood pressure - heart failure from body swelling (fluid retention) - kidney problems including kidney failure - bleeding and ulcers in the stomach and intestine - low red blood cells (anemia) - life-threatening skin reactions - life-threatening allergic reactions - liver problems including liver failure - asthma attacks in people who have asthma | - stomach pain - constipation - diarrhea - gas - heartburn - nausea - vomiting - dizziness

Get emergency help right away if you have any of the following symptoms:

- shortness of breath or trouble breathing
- chest pain
- weakness in one part or side of your body
- slurred speech
- swelling of the face or throat

Stop your NSAID medicine and call your healthcare provider right away if you have any of the following symptoms:

- nausea
- more tired or weaker than usual
- itching
- your skin or eyes look yellow
- stomach pain
- flu-like symptoms
- vomit blood
- there is blood in your bowel movement or it is black and sticky like tar
- unusual weight gain
- skin rash or blisters with fever
- swelling of the arms and legs, hands and feet

These are not all the side effects with NSAID medicines. Talk to your healthcare provider or pharmacist for more information about NSAID medicines.

Call your doctor for medical advice about side effects. You may report side effects to FDA at 1-800-FDA-1088.

Other information about Non-Steroidal Anti-Inflammatory Drugs (NSAIDs)

- Aspirin is an NSAID medicine but it does not increase the chance of a heart attack. Aspirin can cause bleeding in the brain, stomach, and intestines. Aspirin can also cause ulcers in the stomach and intestines.
- Some of these NSAID medicines are sold in lower doses without a prescription (over–the–counter). Talk to your healthcare provider before using over–the–counter NSAIDs for more than 10 days.

NSAID medicines that need a prescription
Generic Name | Tradename
Celecoxib | Celebrex
Diclofenac | Flector, Cataflam, Voltaren, Arthrotec (combined with misoprostol)
Diflunisal | Dolobid
Etodolac | Lodine, Lodine XL
Fenoprofen | Nalfon, Nalfon 200
Flurbirofen | Ansaid
Ibuprofen | Motrin, Tab-Profen, Vicoprofen (combined with hydrocodone), Combunox (combined with oxycodone)
Indomethacin | Indocin, Indocin SR, Indo-Lemmon, Indomethagan
Ketoprofen | Oruvail
Ketorolac | Toradol
Mefenamic Acid | Ponstel
Meloxicam | Mobic
Nabumetone | Relafen
Naproxen | Naprosyn, Anaprox, Anaprox DS, EC-Naproxyn, Naprelan, Naprapac (copackaged with lansoprazole)
Oxaprozin | Daypro
Piroxicam | Feldene
Sulindac | Clinoril
Tolmetin | Tolectin, Tolectin DS, Tolectin 600

This Medication Guide has been approved by the U.S. Food and Drug Administration.

Distributed by: | King Pharmaceuticals Inc. 501 Fifth Street Bristol, TN 37620 USA Telephone: 1-888-840-8884 www.FlectorPatch.com

Manufactured for: IBSA Institut Biochimique SA, CH-6903 Lugano, Switzerland

Manufactured by: Teikoku Seiyaku Co., Ltd., Sanbonmatsu, Kagawa 769-2695 Japan

FI/165 1086

Ed. VII/08.11

Version August, 2011